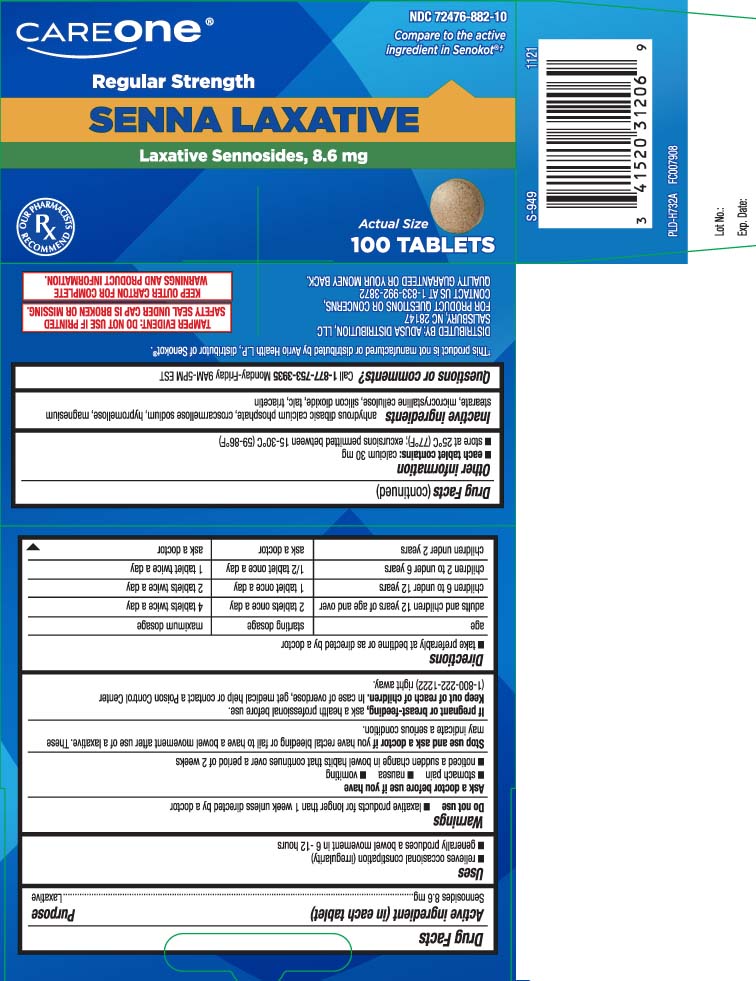 DRUG LABEL: Senna Laxative
NDC: 72476-882 | Form: TABLET
Manufacturer: Care One (Retail Business Services, LLC.)
Category: otc | Type: HUMAN OTC DRUG LABEL
Date: 20240801

ACTIVE INGREDIENTS: SENNOSIDES 8.6 mg/1 1
INACTIVE INGREDIENTS: DIBASIC CALCIUM PHOSPHATE DIHYDRATE; HYPROMELLOSES; MAGNESIUM STEARATE; CROSCARMELLOSE SODIUM; CELLULOSE, MICROCRYSTALLINE; SILICON DIOXIDE; TALC; TRIACETIN

Drug Facts

Active ingredients (in each tablet)

Sennosides 8.6 mg

Purpose

Laxative

Uses

- relieves occasional constipation (irregularity)
- generally produces bowel movement in 6-12 hours

Warnings

Do not use

- laxative products for longer than 1 week unless directed by a doctor

Ask a doctor before use if you have

- stomach pain
- nausea
- vomiting
- noticed a sudden change in bowel habits that continues over a periodof 2 weeks

Stop use and ask a doctor if

you have rectal bleeding or fail to have a bowel movement after use of a laxative. These may indicate a serious condition.

If pregnant or breast-feeding,

ask a health professional before use.

Keep out of reach of children.

In case of overdose, get medical help or contact a Poison Control Center (1-800-222-1222) right away.

Directions

- take preferably at bedtime or as directed by a doctor

age | starting dosage | maximum dosage
adults and children 12 years of age or over | 2 tablets once a day | 4 tablets twice a day
children 6 to under 12 years | 1 tablet once a day | 2 tablets twice a day
children 2 to under 6 years | 1/2 tablet once a day | 1 tablet twice a day
children under 2 years | ask a doctor | ask a doctor

Other information

- each tablet contains: calcium 30 mg
- store at 25ºC (77ºF); excursions permitted between 15-30ºC (59-86ºF)

Inactive ingredients

anhydrous dibasic calcium phosphate, croscarmellose sodium, hypromellose, magnesium stearate, microcrystalline cellulose, silicon dioxide, talc, triacetin

Questions or comments?

Call 1-877-753-3935 Monday-Friday 9AM-5PM EST

Principal Display Panel

Compare to the active ingredients in Senokot®†

Regular Strength

SENNA LAXATIVE

Laxative Sennosides, 8.6 mg

TABLETS

†This product is not manufactured or distributed by Avrio Health L.P., owner of the registered trademark Senokot®.

TAMPER EVIDENT: DO NOT USE IF PRINTED SAFETY SEAL UNDER CAP IS BROKEN OR MISSING.

KEEP OUTER CARTON FOR COMPLETE WARNINGS AND PRODUCT INFORMATION

DISTRIBUTED BY: ADUSA DISTRIBUTION, LLC

SALISBURY, NC 28147

Product Labeling

CAREONE Senna Laxative